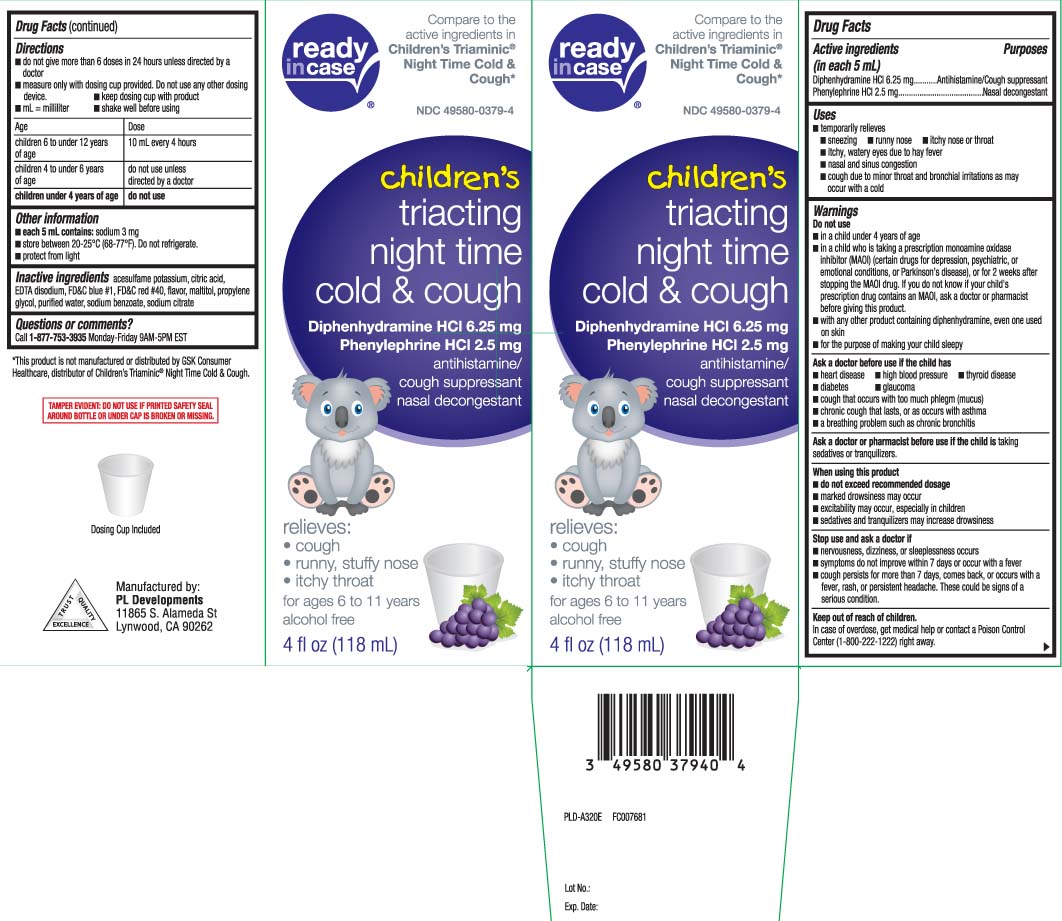 DRUG LABEL: Childrens Triacting Nighttime
NDC: 49580-0379 | Form: LIQUID
Manufacturer: P & L Development, LLC
Category: otc | Type: HUMAN OTC DRUG LABEL
Date: 20231013

ACTIVE INGREDIENTS: PHENYLEPHRINE HYDROCHLORIDE 2.5 mg/5 mL; DIPHENHYDRAMINE HYDROCHLORIDE 6.25 mg/5 mL
INACTIVE INGREDIENTS: ACESULFAME POTASSIUM; SODIUM BENZOATE; ANHYDROUS CITRIC ACID; EDETATE DISODIUM; FD&C RED NO. 40; PROPYLENE GLYCOL; WATER; TRISODIUM CITRATE DIHYDRATE; FD&C BLUE NO. 1; MALTITOL

Drug Facts

Active ingredients (in each 5 mL)

Diphenhydramine HCl 6.25 mg

Phenylephrine HCl 2.5 mg

Purposes

Antihistamine/Cough suppressant

Nasal decongestant

Uses

- temporarily relieves:
  - sneezing
  - runny nose
  - itchy nose or throat
  - itchy, watery eyes due to hay fever
  - nasal and sinus congestion
  - cough due to minor throat and bronchial irritation as may occur with a cold

Warnings

Do not use

- in a child under 4 years of age
- in a child who is taking a prescription monoamine oxidase inhibitor (MAOI) (certain drugs for depression, psychiatric or emotional conditions, or Parkinson’s disease), or for 2 weeks after stopping the MAOI drug. If you do not know if the child’s prescription drug contains an MAOI, ask a doctor or pharmacist before giving this product.
- with any other product containing diphenhydramine, even one used on skin
- for the purpose of making your child sleepy

Ask a doctor before use if the child has

- heart disease
- high blood pressure
- thyroid disease
- diabetes
- glaucoma
- a breathing problem such as chronic bronchitis
- chronic cough that lasts, or as occurs with asthma
- cough that occurs with too much phlegm (mucus)

Ask a doctor or pharmacist before use if the child is

taking sedatives or tranquilizers

When using this product,

- do not exceed recommended dosage
- marked drowsiness may occur
- excitability may occur, especially in children
- sedatives and tranquilizers may increase drowsiness

Stop use and ask a doctor if

- nervousness, dizziness or sleeplessness occurs
- symptoms do not improve within 7 days or occur with a fever
- cough persists for more than 7 days, comes back or occurs with a fever, rash or persistent headache.

These could be signs of a serious condition.

Keep out of reach of children.

In case of overdose, get medical help or contact a Poison Control Center (1-800-222-1222) right away.

Directions

- Do not give more than 6 doses in 24 hours unless directed by a doctor.
- measure only with dosing cup provided. Do not use any other dosing device.
- keep dosing cup with product
- mL = milliliter
- shake well before using

age | dose
children 6 to under 12 years | 10 mL every 4 hours
children 4 to under 6 years | do not use unless directed by a doctor
children under 4 years of age | do not use

Other information

- each 5 mL contains: sodium 3 mg
- store between 20-25°C (68-77°F). Do not refrigerate
- protect from light

Inactive ingredients

acesulfame potassium, anhydrous citric acid, EDTA disodium, FD&C blue #1, FD&C red #40, flavor, maltitol, propylene glycol, purified water, sodium benzoate, trisodium citrate dihydrate

Questions or comments?

Call 1-877-753-3935 Monday-Friday 9AM-5PM EST

Principal Display Panel

Compare to the active ingredients in Children's Triaminic® Nighttime Cold & Cough

children's triacting nighttime

Cold & Cough

Diphenhydramine HCl 6.25 mg

Phenylephrine HCl 2.5 mg

antihistamine/

cough suppressant

nasal decongestant

relieves:

- cough
- runny, stuffy nose
- itchy throat

for ages 6 to 11

Grape Flavor

FL OZ (mL)

*This product is not manufactured or distributed by GSK Consumer Healthcare, distributors of Children's Triaminic® Night Time Cold & Cough.

TAMPER EVIDENT: DO NOT USE IF PRINTED SAFETY SEAL AROUND BOTTLE OR UNDER THE CAP IS BROKEN OR MISSING.

Manufactured by:

PL Developments

11865 S. Alameda St

Lynwood, CA 90262

Package Label

READYinCASE Children's Triacting Night Time Cold and Cough